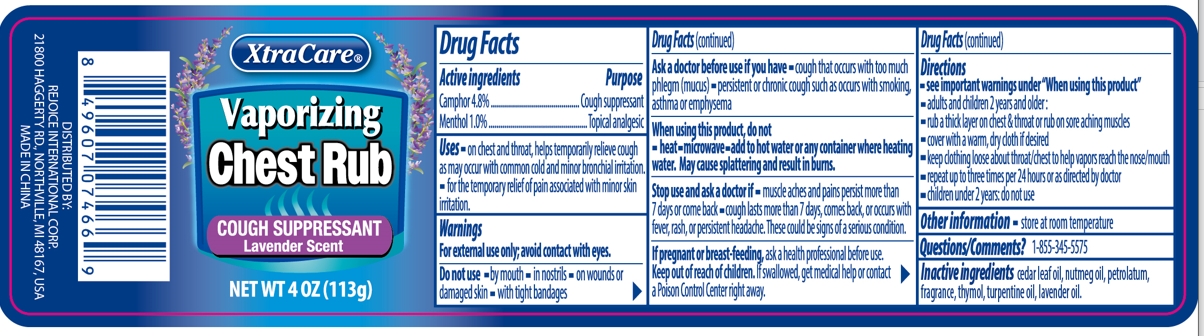 DRUG LABEL: Vaporizing Chest Rub Lavender 4oz
NDC: 57337-160 | Form: OINTMENT
Manufacturer: Rejoice International Corp.
Category: otc | Type: HUMAN OTC DRUG LABEL
Date: 20240201

ACTIVE INGREDIENTS: CAMPHOR (SYNTHETIC) 4.8 g/100 g; MENTHOL 1 g/100 g
INACTIVE INGREDIENTS: PETROLATUM; CEDAR LEAF OIL; THYMOL; NUTMEG OIL; TURPENTINE OIL; LAVENDER OIL

Vaporizing Chest Rub Lavender 4oz

Active ingredients

Camphor 4.8%

Menthol 1.0%

Purpose

Cough suppressant

Topical analgesic

Uses

- Use on chest and throat, helps temporarily relieve cough as may occur with common cold and minor bronchial irritation.
- for the temporary relief of pain associated with minor skin irritation

Warnings

For external use only; avoid contact with eyes.

- Do not use by mouth/in nostrils/ on wounds or damaged skin/ with tight bandages

Ask a doctor before use if you have

- cough that occurs that too much phlegm(mucus)
- persistent ot chronic cough such as occurs with smoking, asthma or emphysema

When using this product, do not

- heat
- microwave
- add to hot water or any container where heating water. May cause splattering and result in burns.

Stop use and ask a doctor if

- muscle aches and pains persist more than 7 days or come back
- cough lasts more than 7 days, comes back, or occurs with fever, rash, or persistent headache. These could be signs of a serious condition

If pregnant or breast-feeding, ask a health professional before use.

Keep out of reach of children. If swallowed, get medical help or contact a Poison Control Center right away.

Directions

- see important warnings under "When using thi sproduct"
- adults and children 2 years older:
- rub a thicj layer on chest & throat or rub on sore aching muscles
- cover with a warm, dry cloth if desired
- keep clothing loose about throat/ chest to help vapors reach the nose/mouth
- repeat up to three times per 24 hours or as directed by doctor
- children under 2 years: do not use

Other information

store at room temperature

Inactive ingredients

cedar leaf oil;nutmeg oil;petrolatum;fragrance; thymol; turpentine oil; lavender oil